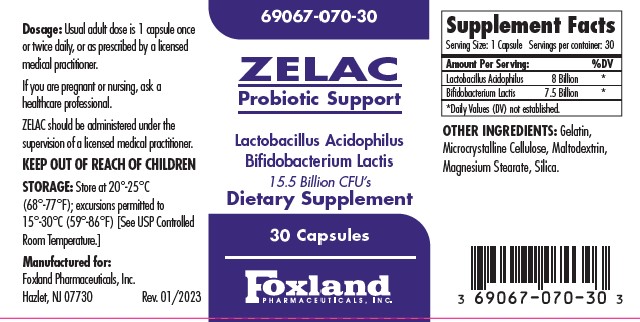 DRUG LABEL: ZELAC 
NDC: 69067-070 | Form: CAPSULE
Manufacturer: Foxland Pharmaceuticals, Inc.
Category: other | Type: DIETARY SUPPLEMENT
Date: 20230220

ACTIVE INGREDIENTS: LACTOBACILLUS ACIDOPHILUS 8000000000 [CFU]/1 1; BIFIDOBACTERIUM ANIMALIS LACTIS 7500000000 [CFU]/1 1
INACTIVE INGREDIENTS: GELATIN, UNSPECIFIED; MICROCRYSTALLINE CELLULOSE; MALTODEXTRIN; MAGNESIUM STEARATE; SILICON DIOXIDE

ZELAC Probiotic Support

STATEMENT OF IDENTITY

Supplement Facts
Serving Size: 1 Capsule | Servings per container: 30
Amount Per Serving: |  | %DV
Lactobacillus Acidophilus | 8 Billion | [Daily Values (DV) not established.]
Bifidobacterium Lactis | 7.5 Billion

OTHER INGREDIENTS: Gelatin, Microcrystalline Cellulose, Maltodextrin, Magnesium Stearate, Silica.

Description

ZELAC capsules is an orally administered prescription probiotic formulation for the clinical dietary management of suboptimal nutritional status in patients where advanced supplementation is required, and maintenance of good health is needed.

Warnings and Precautions

ZELAC capsules should only be used under the directions and supervision of a licensed medical practitioner.

Use with caution in patients that may have a medical condition, are pregnant, lactating, trying to conceive, under the age of 18, or taking other medications.

KEEP OUT OF REACH OF CHILDREN

Dosage and Administration

Usual adult dose is 1 capsule once or twice daily or as prescribed by a licensed medical practitioner.

Precautions

Tamper Evident: Do not use if seal is broken or missing.

Dispensed by Prescription

Storage and Handling

Store at 20°-25°C (68° -77°F); excursions permitted to 15°-30°C (59°- 86°F) [See USP Controlled Room Temperature].

Protect from heat, light and moisture.

PACKAGE LABEL

Add image transcription here...